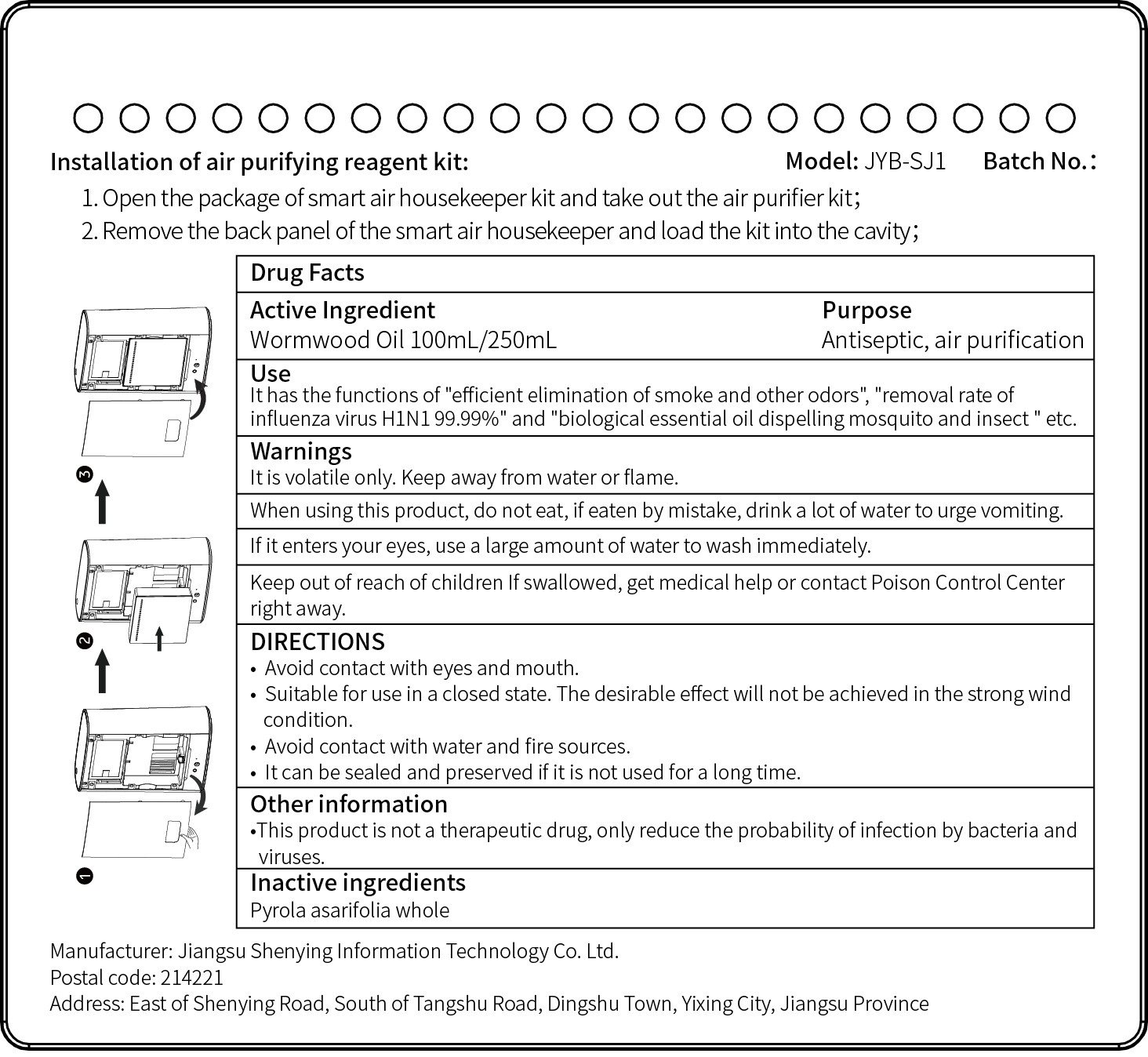 DRUG LABEL: Air Purifying Agent
NDC: 83186-001 | Form: GEL
Manufacturer: Jiangsu Shenying Information Technology Co. Ltd.
Category: homeopathic | Type: HUMAN OTC DRUG LABEL
Date: 20230313

ACTIVE INGREDIENTS: WORMWOOD OIL 100 g/250 mL
INACTIVE INGREDIENTS: EUCALYPTUS OIL; POLYSORBATE 20; LINALOOL, (+)-; PYROLA ASARIFOLIA WHOLE

ACTIVE INGREDIENT

WORMWOOD OIL

PURPOSE

Antiseptic,air purification

Use

lt has the functions of "efficient elimination of smoke and other odors", " removal rate of influenza virus H1N1 99.99%" and "biological essential oil dispelling mosquito and insect " etc.

WARNINGS

lt is volatile only.Keep away from water or flame.

When using this product, do not eat, if eaten by mistake, drink a lot of water to urge vomiting.lf it enters your eyes, use a large amount of water to wash immediately.

Keep out of reach of children lf swallowed,get medical help or contact Poison Control Centerright away.

DOSAGE AND ADMINISTRATION

.Avoid contact with eyes and mouth.
Suitable for use in a closed state.The desirable effect will not be achieved in the strong windcondition.
Avoid contact with water and fire sources.
lt can be sealed and preserved if it is not used for a long time.

Other information

This product is not a therapeutic drug, only reduce the probability of infection by bacteria andviruses.

INACTIVE INGREDIENT

PYROLA ASARIFOLIA WHOLE

EUCALYPTUS OIL

POLYSORBATE 20

LINALOOL